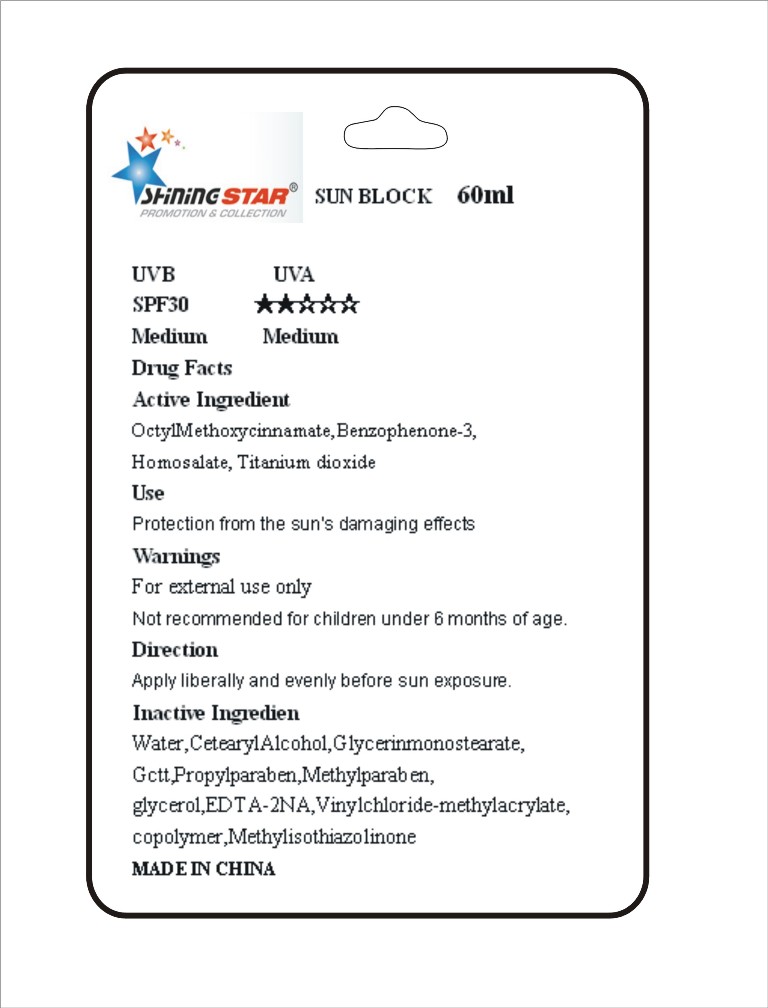 DRUG LABEL: Sun Block
NDC: 51414-200 | Form: CREAM
Manufacturer: Yuyao Jessie Promotional Products Co., Ltd.
Category: otc | Type: HUMAN OTC DRUG LABEL
Date: 20100707

ACTIVE INGREDIENTS: OCTINOXATE 8 mL/100 mL; OXYBENZONE 7.5 mL/100 mL; TITANIUM DIOXIDE 8 mL/100 mL; HOMOSALATE 6 mL/100 mL

Sunblock DRUG FACT

Active Ingredient

OctylMethoxycinnamate,Benzophenone-3,Homosalate, Titanium dioxide

Use

Protection from the sun’s damaging effects

Warnings

For external use only
Not recommended for children under 6 months of age

Direction

Apply liberally and evenly before sun exposure.

Inactive Ingredient

Water,CetearylAlcohol,Glycerinmonostearate,
Gctt,Propylparaben,Methylparaben,
glycerol,EDTA-2NA,Vinylchloride-methylacrylate,
copolymer,Methylisothiazolinone